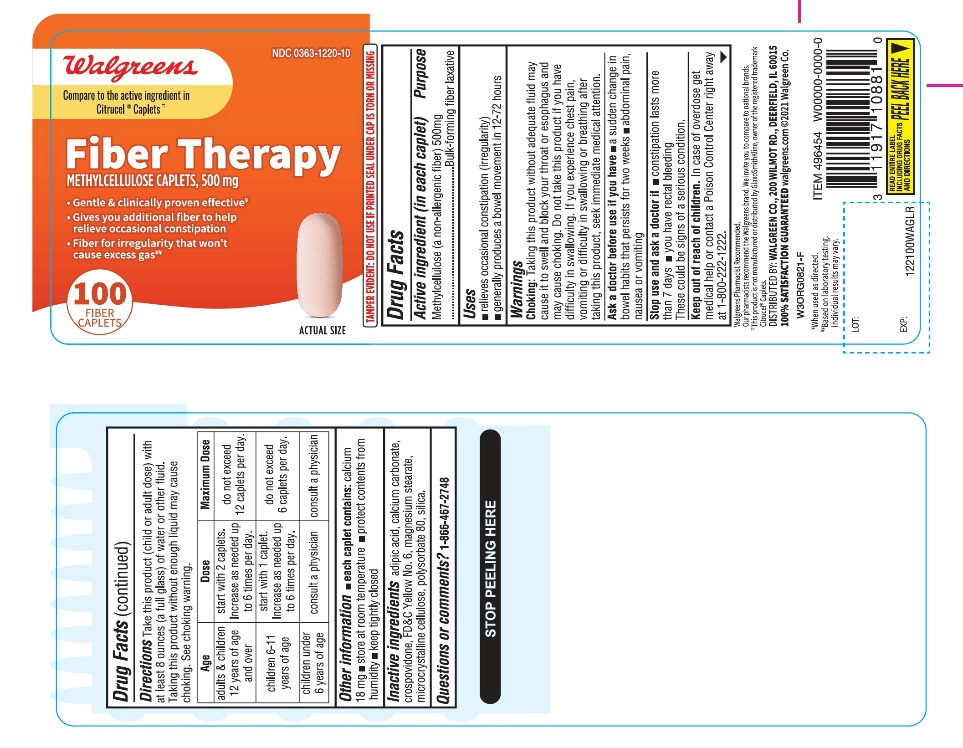 DRUG LABEL: Walgreens

NDC: 0363-1220 | Form: TABLET
Manufacturer: WALGREENS CO.
Category: otc | Type: HUMAN OTC DRUG LABEL
Date: 20251125

ACTIVE INGREDIENTS: METHYLCELLULOSE (4000 MPA.S) 500 mg/1 1
INACTIVE INGREDIENTS: ADIPIC ACID; CALCIUM CARBONATE; CROSPOVIDONE (120 .MU.M); FD&C YELLOW NO. 6; MAGNESIUM STEARATE; MICROCRYSTALLINE CELLULOSE; POLYSORBATE 80; SILICON DIOXIDE

Walgreen Fiber Therapy Methylcellulose 500 mg 100 Caplets

Active ingredient (in each caplet)

Methylcellulose (a non-allergenic fiber) 500mg

Purpose

Bulk-Forming Fiber Laxative

Uses

- helps restore and maintain regularity
- generally, produces a bowel movement in 12 -72 hours.
- relieves occasional constipation (irregularity)

Warnings

Choking: Taking this product without adequate fluid may cause it to swell and block your throat or esophagus and may cause choking .Do not take this product if you have difficulty in swallowing. If you experience chest pain, vomiting or difficulty in swallowing or breathing after taking this product, seek immediate medical attention.

Ask a doctor before use if you have

- a sudden change in bowel habits that persists over a period of two weeks
- abdominal pain, nausea or vomiting

Stop use and ask a doctor if

- constipation lasts more than 7 days
- you have rectal bleeding

These could be signs of a serious condition.

Keep out of reach of children.

In case of overdose, get medical help or contact a Poison Control Center right away at 1-800-222-1222.

Directions

Take this product (child or adult dose) with at least 8 ounces (a full glass) of water or other fluid.

Taking this product without enough liquid may cause choking. See choking warning.

Age | Dose | Maximum Dose
adults & children 12 years of age and over | start with 2 caplets. Increase as needed up to 6 times per day. | Do not exceed 12 caplets per day
Children 6-11 years of age | Start with 1 caplet. Increase as needed up to 6 times per day | Do not exceed 6 caplets per day
children under 6 years of age | Consult a physician | Consult a physician

Other information

- each caplet contains: appx. 18 mg of calcium
- store at room temperature
- protect contents from humidity
- keep tightly closed

Safety sealed: Do not use if printed seal under cap is torn or missing.

Inactive ingredients

adipic acid, calcium carbonate, crospovidone, FD&C yellow no. 6 aluminum lake, magnesium stearate, microcrystalline cellulose, polysorbate 80, silica.

Questions or comments?

1-866-467-2748

Principal Display Panel

Walgreens

NDC# 0363-1220-10

Compare to Citrucel®active ingredients††

Fiber Therapy

METHYLCELLULOSE CAPLETS, 500 mg

FIBER CAPSULES FOR REGULARITY

- Daily source 100% Soluble Fiber
- 100 FIBER CAPLETS
- GLUTEN FREE

Walgreens Pharmacist Recommended

Walgreens Pharmacist Survey

††This product is not manufactured or distributed by GlaxoSmithKline, the distributor of CITRUCEL® Caplets.

DISTRIBUTED BY: WALGREEN CO., 200 WILMOT RD., DEERFIELD, IL 60015

100 % SATISFACTION GUARANTEED walgreens.com ©2018 Walgreen Co.